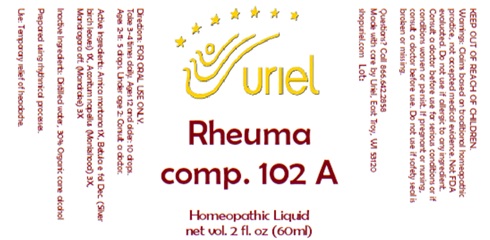 DRUG LABEL: Rheuma comp. 102 A
NDC: 48951-8432 | Form: LIQUID
Manufacturer: Uriel Pharmacy. Inc
Category: homeopathic | Type: HUMAN OTC DRUG LABEL
Date: 20241220

ACTIVE INGREDIENTS: ACONITUM NAPELLUS 3 [hp_X]/1 mL; MANDRAGORA OFFICINARUM ROOT 3 [hp_X]/1 mL; ARNICA MONTANA FLOWER 1 [hp_X]/1 mL; BETULA PUBESCENS LEAF 1 [hp_X]/1 mL
INACTIVE INGREDIENTS: ALCOHOL; WATER

Rheuma comp. 102 A

INDICATIONS AND USAGE

Directions: FOR ORAL USE ONLY.

DOSAGE AND ADMINISTRATION

Take 3-4 times daily. Ages 12 and older: 10 drops.
Ages 2-11: 5 drops. Under age 2: Consult a doctor.

ACTIVE INGREDIENT

Active Ingredients: Arnica montana 1X, Betula e fol Dec. (Silver birch leaves) 1X, Aconitum napellus (Monkshood) 3X, Mandragora off. (Mandrake) 3X

Inactive Ingredients: Distilled water, 30% Organic cane alcohol

Prepared using rhythmical processes.

PURPOSE

Use: Temporary relief of headache.

KEEP OUT OF REACH OF CHILDREN.

WARNINGS

Warnings: Claims based on traditional homeopathic practice, not accepted medical evidence. Not FDA evaluated. Do not use if allergic to any ingredient. Consult a doctor before use for serious conditions or if conditions worsen or persist. If pregnant or nursing, consult a doctor before use. Do not use if safety seal is broken or missing.

Questions? Call 866.642.2858
Made with care by Uriel, East Troy, WI 53120
shopuriel.com Lot: